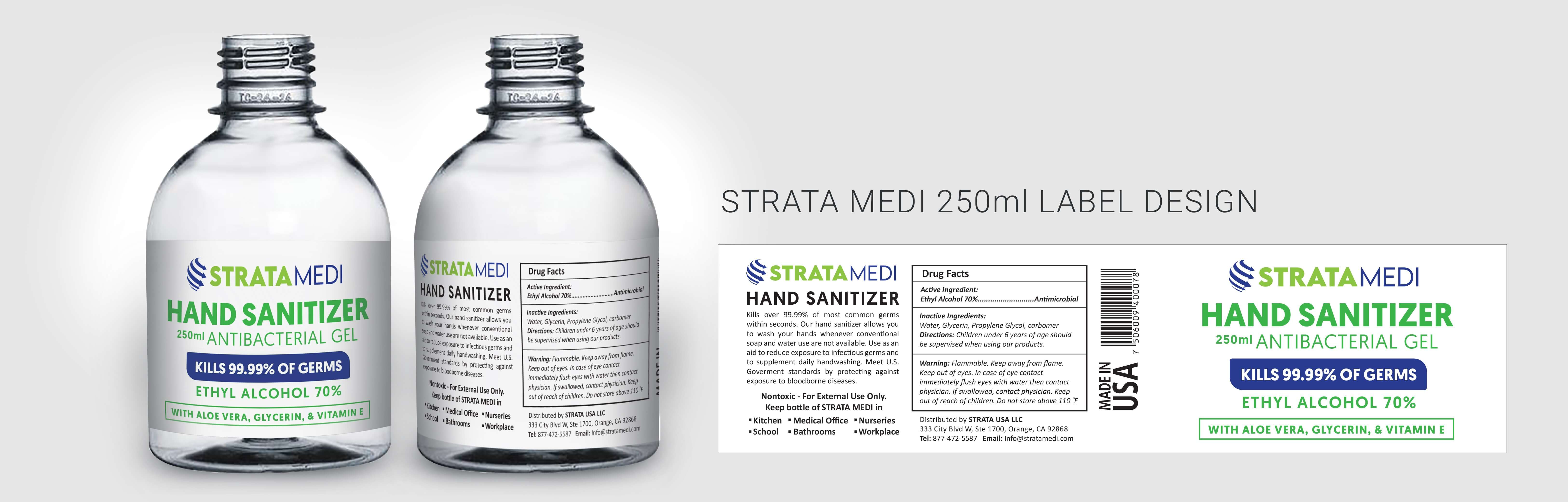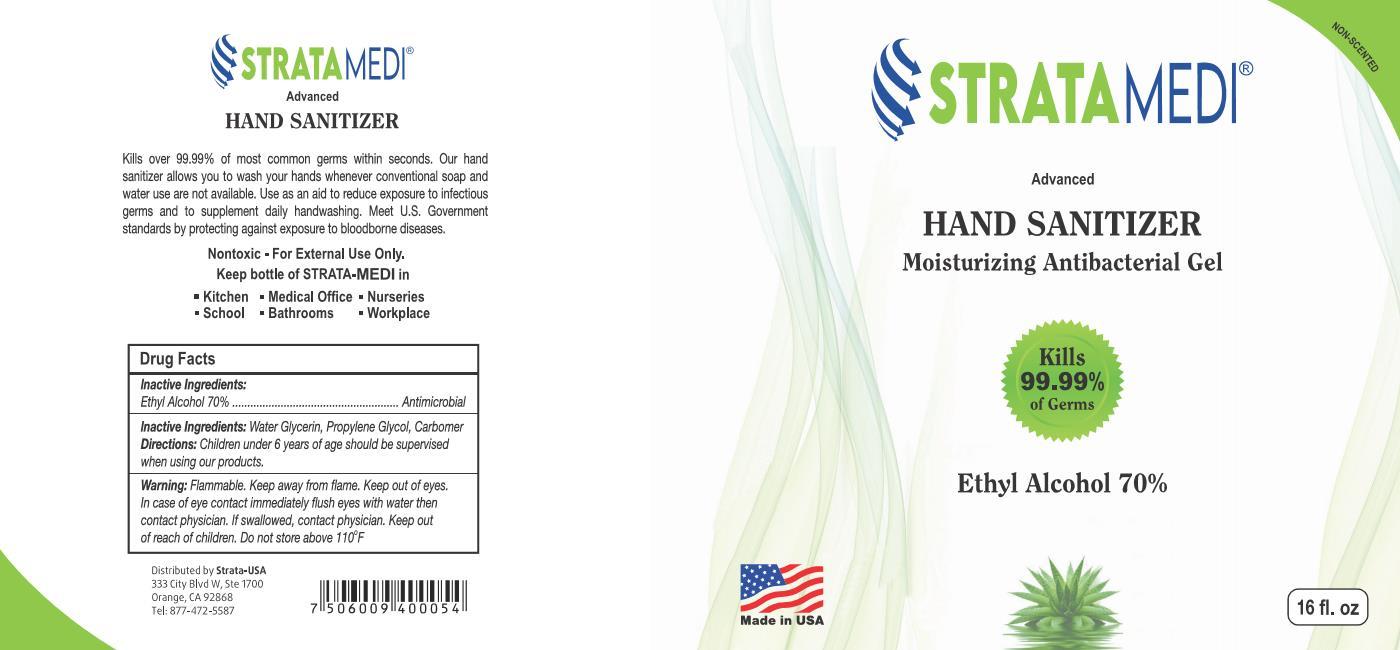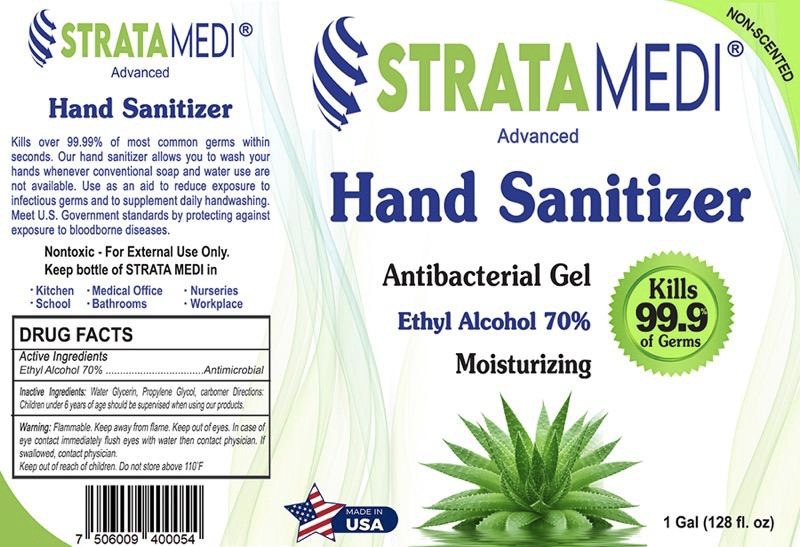 DRUG LABEL: STRATAMEDI Hand Sanitizer Antibacterial Gel
NDC: 77004-202 | Form: GEL
Manufacturer: Strata USA LLC
Category: otc | Type: HUMAN OTC DRUG LABEL
Date: 20200531

ACTIVE INGREDIENTS: ALCOHOL 70 mL/100 mL
INACTIVE INGREDIENTS: WATER; GLYCERIN 0.7 mL/100 mL; CARBOMER 940 0.2 mL/100 mL; PROPYLENE GLYCOL 0.4 mL/100 mL; AMINOMETHYLPROPANOL 0.1 mL/100 mL

STRATAMEDI Ethyl Alcohol Sanitizer

PURPOSE

Hand Sanitizer. Kills over 99.99% of most common germs within seconds. Our Sanitizer allows you to wash your hands whenever conventional soap and water are not avialble. Use as an aid to reduce exposure to infectious germs and to supplement daily handwashing..Meet US Government standards by protecting against exposure to bloodborne diseases

ACTIVE INGREDIENT

Ethyl Alcohol 70%...........................Antimicrobial

INACTIVE INGREDIENT

Water, Glycerin, Propylene Glycol, Carbomer

WARNINGS

Flammable. Keep away from flame. Keep out of eyes. In case of eye contact immediately flush eyes with water then contact physician. If swallowed, contact physician. Keep out of reach of children. Do not store above 110°F

Keep out of reach of children

DOSAGE AND ADMINISTRATION

Children under 6 years of age should be supervised when using our products

INDICATIONS AND USAGE

Hand Sanitizer

PACKAGE LABEL

250 mL NDC 77004-20141

PACKAGE LABEL

3885 ml NDC 77004-2014-3